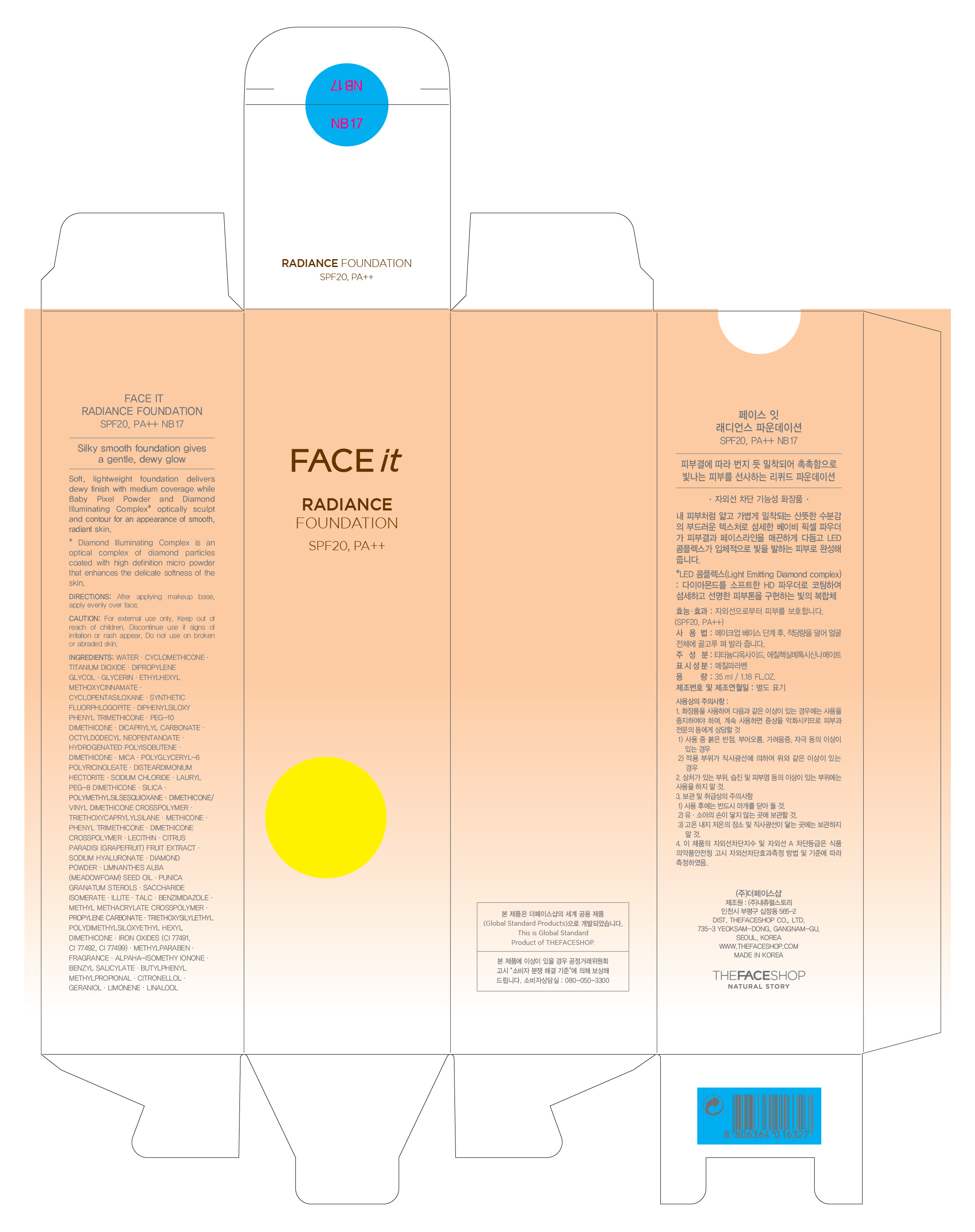 DRUG LABEL: FACE IT RADIANCE POWDER PACT SPF25 MOISTURE VEIL NB17
NDC: 51523-117 | Form: CREAM
Manufacturer: THEFACESHOP CO., LTD
Category: otc | Type: HUMAN OTC DRUG LABEL
Date: 20110909

ACTIVE INGREDIENTS: OCTINOXATE 4 mL/100 mL; TITANIUM DIOXIDE 6.208 mL/100 mL; ZINC OXIDE 1.96 mL/100 mL
INACTIVE INGREDIENTS: WATER; TRIETHOXYCAPRYLYLSILANE; TALC; MICA; SILICON DIOXIDE; BARIUM SULFATE; TRIETHYLHEXANOIN; MAGNESIUM MYRISTATE; DIMETHICONE; FERRIC OXIDE YELLOW; METHYLPARABEN; FERRIC OXIDE RED; CALCIUM CARBONATE; BUTYLPARABEN; FERROSOFERRIC OXIDE; HAEMATOCOCCUS PLUVIALIS; BUTYLENE GLYCOL; ASTAXANTHIN; CAMELLIA JAPONICA SEED; LILIUM CANDIDUM FLOWER; LEONTOPODIUM ALPINUM FLOWERING TOP; NELUMBO NUCIFERA FLOWER; JASMINUM OFFICINALE FLOWER; NARCISSUS PSEUDONARCISSUS FLOWER

FACE IT RADIANCE POWDER PACT SPF25, PA++ MOISTURE VEIL NB17

ACTIVE INGREDIENT

OCTINOXATE (4%)
TITANIUM DIOXIDE (6.208%)
Zinc Oxide (1.96%)

INACTIVE INGREDIENT

WATER
TRIETHOXYCAPRYLYLSILANE
TALC
MICA
SILICON DIOXIDE
BARIUM SULFATE
TRIETHYLHEXANOIN
MAGNESIUM MYRISTATE
DIMETHICONE
FERRIC OXIDE YELLOW
METHYLPARABEN
FERRIC OXIDE RED
CALCIUM CARBONATE
BUTYLPARABEN
FERROSOFERRIC OXIDE
HAEMATOCOCCUS PLUVIALIS
BUTYLENE GLYCOL
ASTAXANTHIN
CAMELLIA JAPONICA SEED
LILIUM CANDIDUM FLOWER
LEONTOPODIUM ALPINUM FLOWERING TOP
NELUMBO NUCIFERA FLOWER
JASMINUM OFFICINALE FLOWER
NARCISSUS PSEUDONARCISSUS FLOWER

PURPOSE

Provides high protection against sunburn and tanning.

WHEN USING

Avoid contact with eyes.

STOP USE

Discontinue use if sign of irritation or rash appear.

DOSAGE AND ADMINISTRATION

Dispense an adequate amount and apply evenly. (At the final stage of basic skincare, dispense an adequate amount and apply evenly to desired parts)

PACKAGE LABEL

FACE IT RADIANCE POWDER PACT SPF25 MOISTURE VEIL NB17